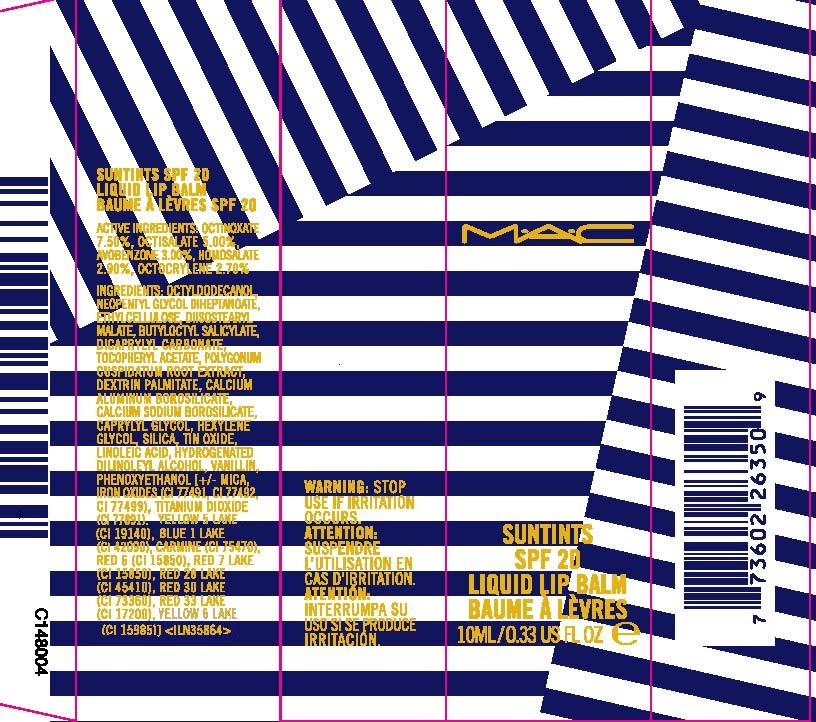 DRUG LABEL: SUNTINTS
NDC: 40046-0034 | Form: LIPSTICK
Manufacturer: MAKEUP ART COSMETICS
Category: otc | Type: HUMAN OTC DRUG LABEL
Date: 20120426

ACTIVE INGREDIENTS: OCTINOXATE 7.5 mL/100 mL; OCTISALATE 5.0 mL/100 mL; AVOBENZONE 3.0 mL/100 mL; HOMOSALATE 2.9 mL/100 mL; OCTOCRYLENE 2.7 mL/100 mL
INACTIVE INGREDIENTS: OCTYLDODECANOL; NEOPENTYL GLYCOL DIHEPTANOATE; ETHYLCELLULOSES; DIISOSTEARYL MALATE; BUTYLOCTYL SALICYLATE; DICAPRYLYL CARBONATE; ALPHA-TOCOPHEROL ACETATE; POLYGONUM CUSPIDATUM ROOT; CALCIUM ALUMINOSILICATE; CAPRYLYL GLYCOL; HEXYLENE GLYCOL; SILICON DIOXIDE; STANNIC OXIDE; LINOLEIC ACID; VANILLIN; PHENOXYETHANOL; FERRIC OXIDE RED; MICA; TITANIUM DIOXIDE; FD&C BLUE NO. 1; COCHINEAL; D&C RED NO. 6; D&C RED NO. 7; D&C RED NO. 28; D&C RED NO. 30; D&C RED NO. 33; FD&C YELLOW NO. 5

ACTIVE INGREDIENT

ACTIVE INGREDIENTS: OCTINOXATE 7.50% [] OCTISALATE 5.00% [] AVOBENZONE 3.00% [] HOMOSALATE 2.90% [] OCTOCRYLENE 2.70%

INACTIVE INGREDIENT

INACTIVE INGREDIENTS: OCTYLDODECANOL [] NEOPENTYL GLYCOL DIHEPTANOATE [] ETHYLCELLULOSE [] DIISOSTEARYL MALATE [] BUTYLOCTYL SALICYLATE [] DICAPRYLYL CARBONATE [] TOCOPHERYL ACETATE [] POLYGONUM CUSPIDATUM ROOT EXTRACT [] DEXTRIN PALMITATE [] CALCIUM ALUMINUM BOROSILICATE [] CALCIUM SODIUM BOROSILICATE [] CAPRYLYL GLYCOL [] HEXYLENE GLYCOL [] SILICA [] TIN OXIDE [] LINOLEIC ACID [] HYDROGENATED DILINOLEYL ALCOHOL [] VANILLIN [] PHENOXYETHANOL [] [+/- MICA [] IRON OXIDES (CI 77491, CI 77492, CI 77499) [] TITANIUM DIOXIDE (CI 77891) [] BISMUTH OXYCHLORIDE (CI 77163) [] BLUE 1 LAKE (CI 42090) [] CARMINE (CI 75470) [] RED 6 (CI 15850) [] RED 7 LAKE (CI 15850) [] RED 28 LAKE (CI 45410) [] RED 30 LAKE (CI 73360) [] RED 33 LAKE (CI 17200) [] YELLOW 5 LAKE (CI 19140) [] YELLOW 6 LAKE (CI 15985)]

WARNINGS

WARNING: STOP USE IF IRRITATION OCCURS.

PACKAGE LABEL

MAC

SUNTINTS SPF 20

LIQUID BALM

10 ML/ .33 FL OZ LIQ

MAKE UP ART COSMETICS, DIST

NY,NY 10022